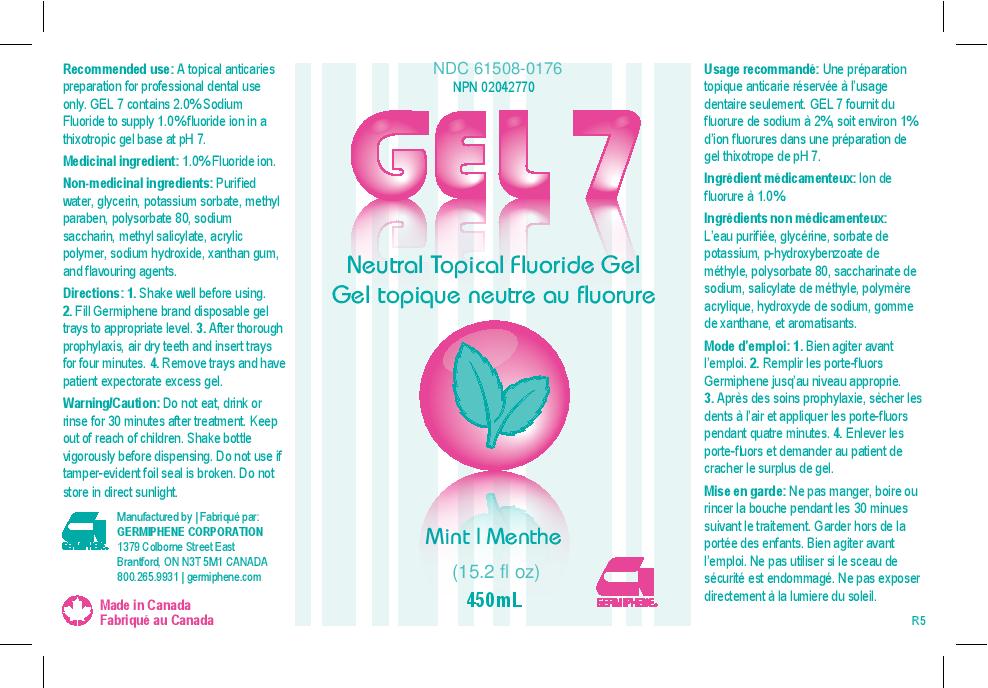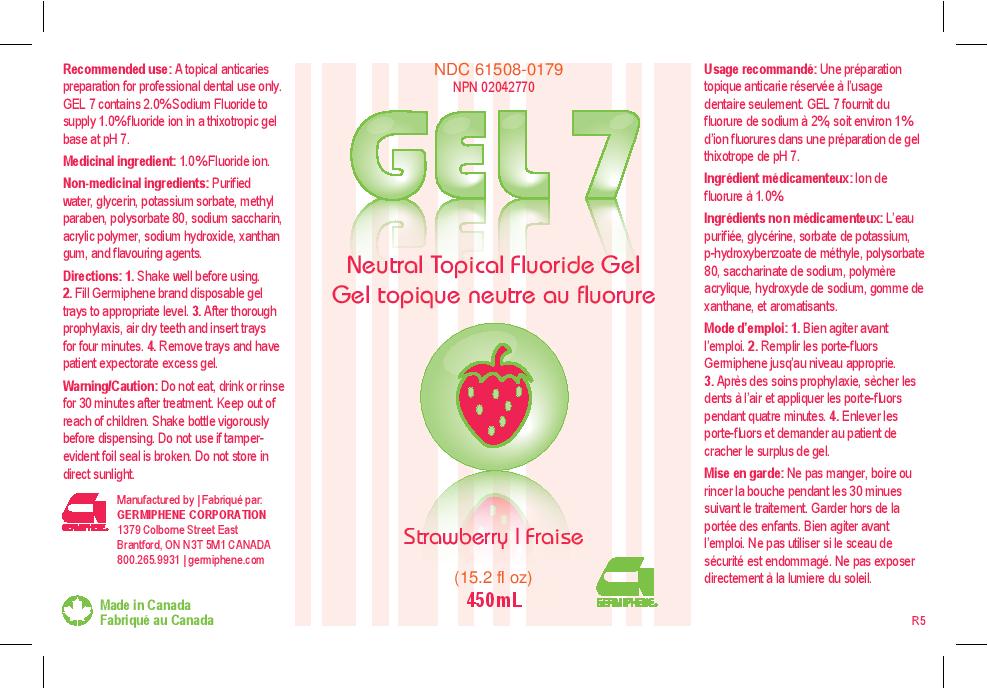 DRUG LABEL: Gel 7 Neutral Topical Fluoride Gel Mint
NDC: 61508-0176 | Form: GEL, DENTIFRICE
Manufacturer: Germiphene Corporation
Category: otc | Type: HUMAN OTC DRUG LABEL
Date: 20170201

ACTIVE INGREDIENTS: SODIUM FLUORIDE 2 g/100 g
INACTIVE INGREDIENTS: SACCHARIN SODIUM 0.3 g/100 g; METHYLPARABEN 0.08 g/100 g; POTASSIUM SORBATE 0.1 g/100 g; GLYCERIN 7 g/100 g; SPEARMINT 1 g/100 g; METHYL SALICYLATE 0.1 g/100 g; CARBOXYPOLYMETHYLENE 1 g/100 g; POLYSORBATE 80 0.1 g/100 g; WATER 86.9 g/100 g; XANTHAN GUM 1 g/100 g; SODIUM HYDROXIDE 0.425 g/100 g

Gel 7 Topical Fluoride Gel

Recommended Use:

A topical anticaries preparation for professional dental use only.

PURPOSE

Gel 7 contains 2.0% sodium fluoride to supply 1.0% fluoride ion in a thixotropic gel base at pH 7.

Medicinal Ingredient:

1.0 % Fluoride ion

Non-medicinal ingredients:

Purified water, glycerin, potassium sorbate, methyl paraben, polysorbate 80, sodium saccharin, methyl salcylate, acrylic polymer, sodium hydroxide, xanthan gum, and flavouring agents.

Directions:

1. Shake well before using. 2. Fill Germiphene brand disposable gel trays to appropriate level. 3. After thorough prophylaxis, air dry teeth and insert trays for four minutes. 4. Remove trays and have patient expectorate excess gel.

Keep out of reach of children.

Warning/Caution:

Do not eat, drink, or rinse for 30 minutes after treatment. Shake bottle vigorously before dispensing. Do not use if tamper-evident foil seal is broken. Do not store in direct sunlight.

PACKAGE LABEL

450 mL (15.2 fl oz)